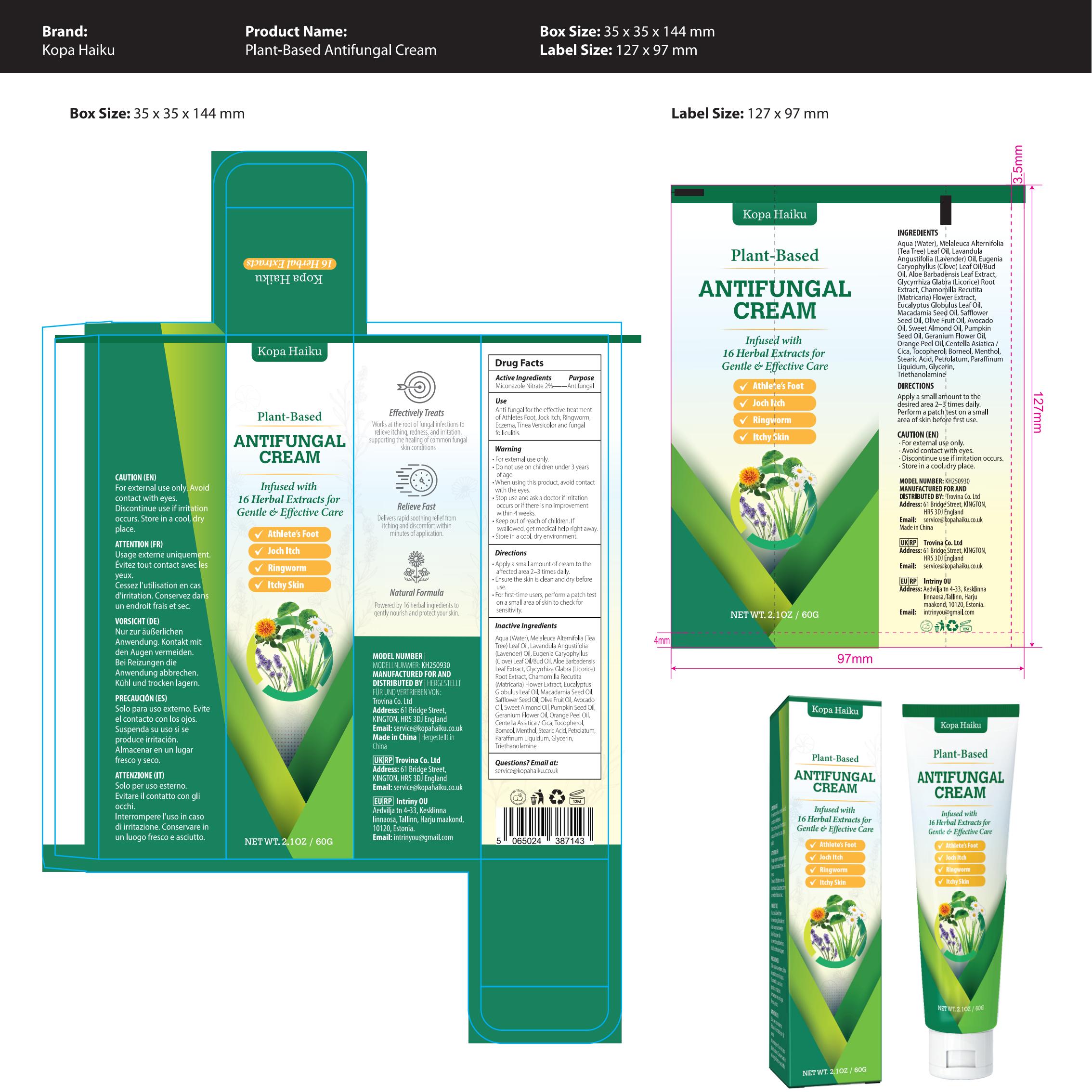 DRUG LABEL: Kopa Haiku Antifungal Cream
NDC: 87041-004 | Form: CREAM
Manufacturer: Trovina Co. Ltd
Category: otc | Type: HUMAN OTC DRUG LABEL
Date: 20260212

ACTIVE INGREDIENTS: MICONAZOLE NITRATE 20 mg/1 g
INACTIVE INGREDIENTS: ORANGE OIL; PETROLATUM; ALOE BARBADENSIS LEAF POWDER; TOCOPHEROL; CENTELLA ASIATICA; SAFFLOWER SEED OIL POLYGLYCERYL-6 ESTERS; ALMOND OIL; PUMPKIN SEED OIL; HYDROGENATED MACADAMIA SEED OIL; GLYCERIN; LAVANDULA ANGUSTIFOLIA (LAVENDER) OIL; AQUA; EUGENIA CARYOPHYLLUS (CLOVE) LEAF OIL; STEARIC ACID; AVOCADO OIL; BORNEOL; EUGENIA CARYOPHYLLUS (CLOVE) BUD OIL; GLYCYRRHIZA GLABRA (LICORICE) ROOT POWDER; MELALEUCA ALTERNIFOLIA (TEA TREE) LEAF OIL; CHAMOMILE; PELARGONIUM GRAVEOLENS FLOWER OIL; PARAFFINUM LIQUIDUM; TRIETHANOLAMINE; MENTHOL; EUCALYPTUS GLOBULUS LEAF OIL; OLIVE OIL

ACTIVE INGREDIENT

Miconazole Nitrate 2%

PURPOSE

Antifungal

INDICATIONS AND USAGE

Anti-fungal for the effective treatment of Athlete's Foot, Jock Itch, Ringworm, Eczema, Tinea Versicolor, and fungal folliculitis.

WARNINGS

For external use only

DO NOT USE

On children under 3 years of age.

OTHER SAFETY INFORMATION

Avoid contact with the eyes.

STOP USE

Irritation occurs or if there is no improvement within 4 weeks.

Keep out of reach of children. In case of ingestion, seek medical help or contact a Poison Control Center immediately.

DOSAGE AND ADMINISTRATION

1 Apply a small amount of cream to the affected area 2-3 times daily; 2 Ensure the skin in clean and dry before use; 3 For first-time users, perform a patch test on a small area of skin to check for sensitivity.

STORAGE AND HANDLING

Store in a cool, dry place.

INACTIVE INGREDIENT

Aqua (Water), Melaleuca Alternifolia (Tea Tree) Leaf Oil, Lavandula Angustifolia (Lavender) Oil, Eugenia Caryophyllus (Clove) Leaf Oil/Bud Oil, Aloe Barbadensis Leaf Extract, Glycyrrhiza Glabra (Licorice) Root Extract, Chamomilla Recutita (Matricaria) Flower Extract, Eucalyptus Globulus Leaf Oil, Macadamia Seed Oil, Safflower Seed Oil, Olive Fruit Oil, Avocado Oil, Sweet Almond Oil, Pumpkin Seed Oil, Geranium Flower Oil, Orange Peel Oil, Centella Asiatica (Cica), Tocopherol, Borneol, Menthol, Stearic Acid, Petrolatum, Paraffinum Liquidum, Glycerin, Triethanolamine

QUESTIONS

Email at: service@kopahaiku.co.uk